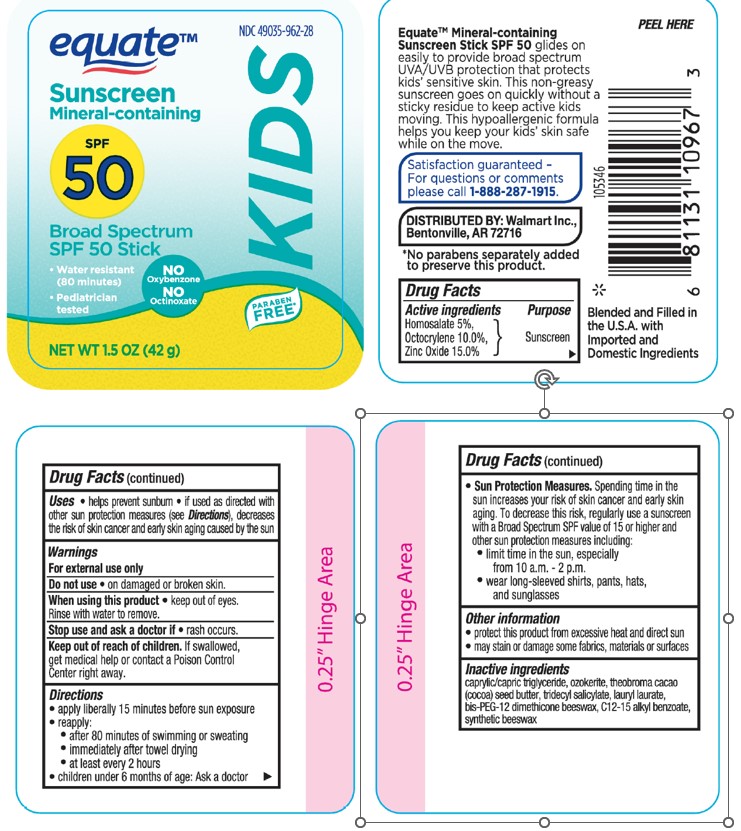 DRUG LABEL: Equate Sunscreen Mineral Based KIDS Broad Spectrum spf 50
NDC: 49035-962 | Form: STICK
Manufacturer: Wal-Mart Stores Inc
Category: otc | Type: HUMAN OTC DRUG LABEL
Date: 20241016

ACTIVE INGREDIENTS: HOMOSALATE 50 mg/1 g; OCTOCRYLENE 100 mg/1 g; ZINC OXIDE 150 mg/1 g
INACTIVE INGREDIENTS: MEDIUM-CHAIN TRIGLYCERIDES; COCOA BUTTER; LAURYL LAURATE; ALKYL (C12-15) BENZOATE; TRIDECYL SALICYLATE; SYNTHETIC BEESWAX; CERESIN

Equate Sunscreen Mineral Based Kids Broad Spectrum SPF 50

Active ingredients

Homosalate 5.0%,

Octocrylene 10.0%,

Zinc Oxide 15.0%

Purpose

Sunscreen

Uses

• helps prevent sunburn • if used as directed with other sun protection measures (see Directions), decreases the risk of skin cancer and early skin aging caused by the sun

Warnings

For external use only

Do not use

•on damaged or broken skin.

When using this product

• keep out of eyes. Rinse with water to remove.

Stop use and ask a doctor if

• rash occurs.

Keep out of reach of children

If product is swallowed, get medical help or contact a Poison Control Poison Control Center right away.

Directions

• apply liberally 15 minutes before sun exposure

• reapply:

• after 80 minutes of swimming or sweating

• immediately after towel drying

• at least every 2 hours

• children under 6 months of age: Ask a doctor

• Sun Protection Measures. Spending time in the sun increases your risk of skin cancer and early skin aging. To decrease this risk, regularly use a sunscreen with a Broad Spectrum SPF value of 15 or higher and other sun protection measures including:

• limit time in the sun, especially from 10 a.m. - 2 p.m.

• wear long-sleeved shirts, pants, hats, and sunglasses

Other information

• protect the product in this container from excessive heat and direct sun

• may stain or damage some fabrics, materials or surfaces

Inactive ingredients

caprylic/capric triglyceride, ozokerite, theobroma cacao (cocoa) seed butter, tridecyl salicylate, lauryl laurate bis-PEG-12 dimethicone beeswax, C12-15 alkyl benzoate, synthetic beeswax